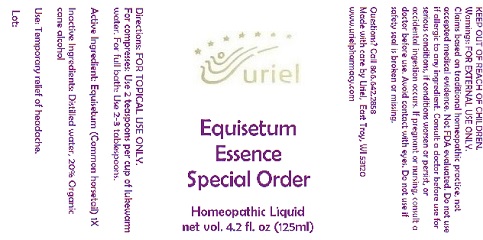 DRUG LABEL: Equisetum Essence Special Order
NDC: 48951-4136 | Form: LIQUID
Manufacturer: Uriel Pharmacy Inc.
Category: homeopathic | Type: HUMAN OTC DRUG LABEL
Date: 20180504

ACTIVE INGREDIENTS: EQUISETUM ARVENSE TOP 1 [hp_X]/1 mL
INACTIVE INGREDIENTS: WATER; ALCOHOL

Equisetum Essence Special Order

INDICATIONS AND USAGE

Directions: FOR TOPICAL USE ONLY.

DOSAGE AND ADMINISTRATION

For compresses: Use 2 teaspoons per cup of lukewarm water. For full bath: Use 2-3 tablespoons.

Active Ingredient: Equisetum (Common horsetail) 1X

Inactive Ingredients: Distilled water, 20% Organic cane alcohol

PURPOSE

Use: Temporary relief of headache.

KEEP OUT OF REACH OF CHILDREN.

Warnings: FOR EXTERNAL USE ONLY.
Claims based on traditional homeopathic practice, not accepted medical evidence. Not FDA evaluated. Do not use if allergic to any ingredient. Consult a doctor before use for serious conditions, if conditions worsen or persist, or accidental ingestion occurs. If pregnant or nursing, consult a doctor before use. Avoid contact with eyes. Do not use if safety seal is broken or missing.

Questions? Call 866.642.2858
Made with care by Uriel, East Troy, WI 53120
www.urielpharmacy.com